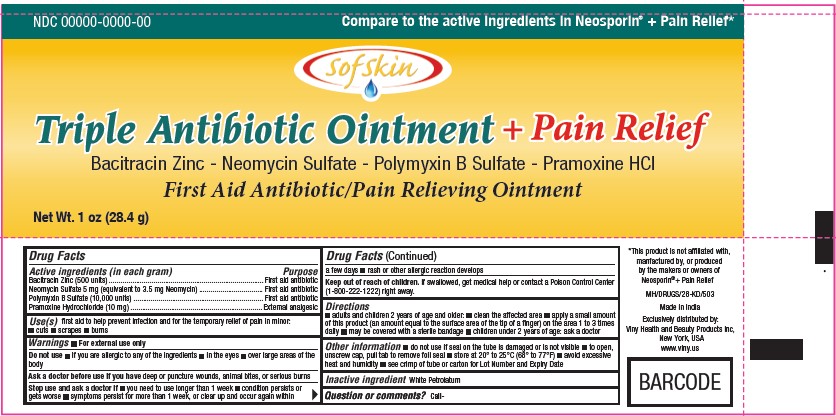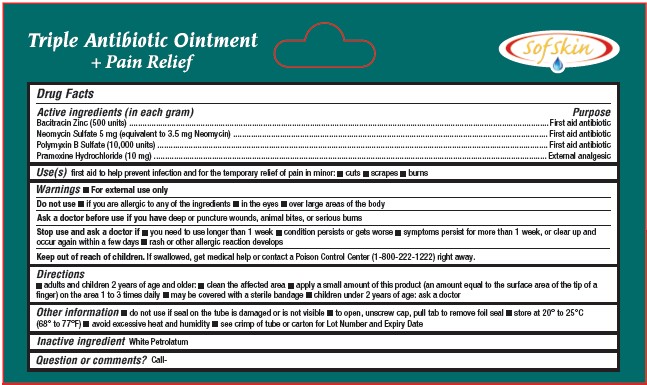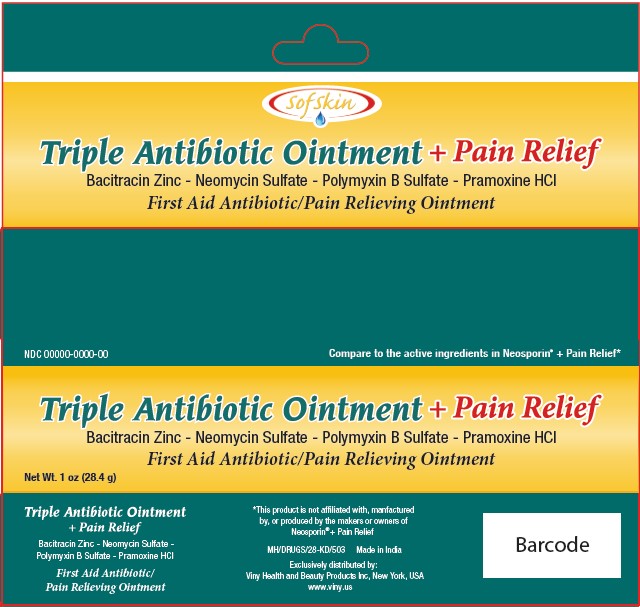 DRUG LABEL: SOFSKIN TRIPLE ANTIBIOTIC
NDC: 61040-134 | Form: OINTMENT
Manufacturer: GOPALDAS VISRAM AND COMPANY LIMITED
Category: otc | Type: HUMAN OTC DRUG LABEL
Date: 20241210

ACTIVE INGREDIENTS: PRAMOXINE HYDROCHLORIDE 10 mg/1 g; BACITRACIN ZINC 500 [USP'U]/1 g; NEOMYCIN SULFATE 5 mg/1 g; POLYMYXIN B SULFATE 10000 [USP'U]/1 g
INACTIVE INGREDIENTS: WHITE PETROLATUM

Gopaldas (as CMO) - SOFSKIN TRIPLE ANTIBIOTIC OINTMENT + PAIN RELIEF (61040-134)

ACTIVE INGREDIENTS

Bacitracin Zinc (500 units)
Neomycin Sulfate 5 mg (equivalent to 3.5 mg Neomycin)
Polymyxin B Sulfate (10,000 units)
Pramoxine Hydrochloride (10 mg)

PURPOSE

First aid antibiotic
First aid antibiotic
First aid antibiotic
External analgesic

USES

First aid to help prevent infection and for the temporary relief of pain in minor:

- cuts
- scrapes
- burns

WARNINGS

- For external use only.

Do not use

- if you are allergic to any of the ingredients
- in the eyes
- over large areas of the body

Ask a doctor before use if you have deep or puncture wounds, animal bites, or serious burns.

Stop use and ask a doctor if

- you need to use longer than 1 week
- condition persists or gets worse
- symptoms persist for more than 1 week, or clear up and occur again within a few days
- rash or other allergic reaction develops

Keep out of reach of children. If swallowed, get medical help or contact a Poison Control Center (1-800-222-1222) right away.

DIRECTIONS

- adults and children 2 years of age and older:
- clean the affected area
- apply a small amount of this product (an amount equal to the surface area of the tip of a finger) on the area 1 to 3 times daily
- may be covered with a sterile bandage
- children under 2 years of age: ask a doctor

OTHER INFORMATION

- do not use if seal on the tube is damaged or is not visible
- to open, unscrew cap, pull tab to remove foil seal
- store at 20° to 25°C (68° to 77°F)
- avoid excessive heat and humidity
- see crimp of tube or carton for Lot Number and Expiry Date

INACTIVE INGREDIENT

WHITE PETROLATUM